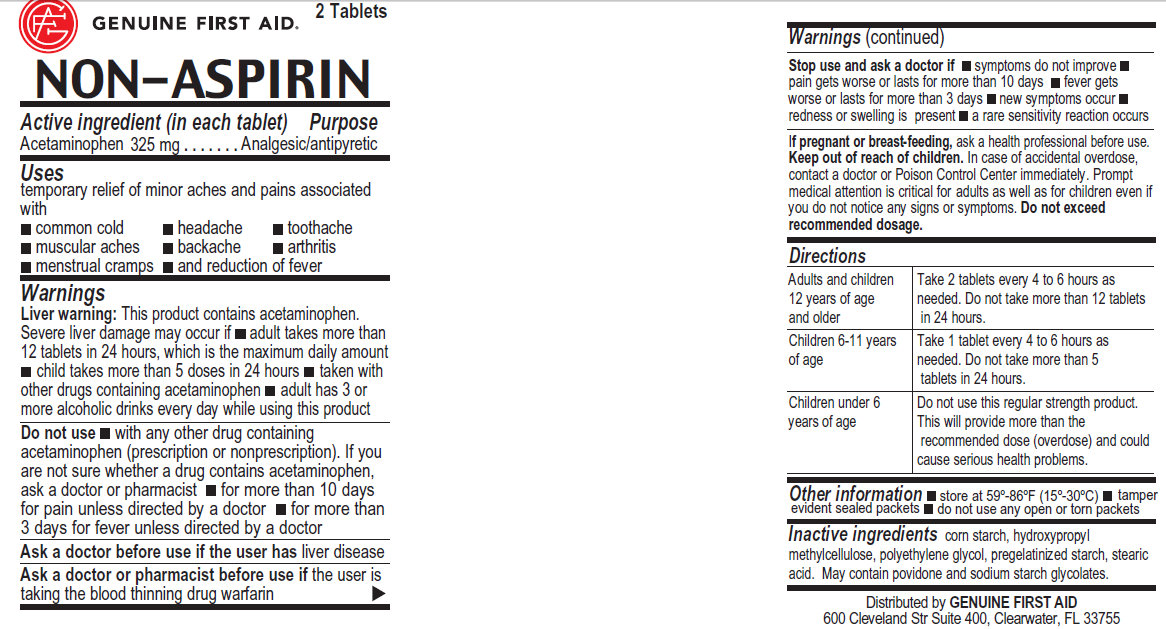 DRUG LABEL: NON-ASPIRIN

NDC: 52124-0010 | Form: TABLET
Manufacturer: Genuine First Aid LLC
Category: otc | Type: HUMAN OTC DRUG LABEL
Date: 20171230

ACTIVE INGREDIENTS: ACETAMINOPHEN 325 mg/1 1
INACTIVE INGREDIENTS: STARCH, CORN; POLYETHYLENE GLYCOL; STEARIC ACID; POVIDONE

NON-ASPIRIN Acetaminophen 325mg

Active Ingredient (in each tablet)

Acetaminophen 325 mg

Purpose

Analgesic/antipyretic

Uses

temporary relief of minor aches and pains associated with:

common cold; headache; toothache; muscular aches; backache; arthritis; menstrual cramps; and reduction of fever

Warnings

Liver warning: This product contains acetaminophen.

Severe liver damage may occur if: adult takes more than 12 tablets in 24 hours, which is the maximum daily amount; child takes more than 5 doses in 24 hours; taken with other drugs containing acetaminophen; adult has 3 or more alcoholic drinks every day while using this product

Do not use

with any other drug containing acetaminophen (prescription or nonprescription). If you are not sure whether a drug contains acetaminophen, ask a doctor or pharmacist; for more than 10 days for pain unless directed by a doctor; for more than 3 days for fever unless directed by a doctor

Ask a doctor before use if the user has liver disease

Ask a doctor or pharmacist before use if the user is taking the blood thinning drug warfarin

Stop use and ask a doctor if: symptoms do not improve; pain gets worse or lasts for more than 10 days; fever gets worse or lasts for more than 3 days; new symptoms occur; redness or swelling is present; a rare sensitivity reaction occurs

PREGNANCY OR BREAST FEEDING

If pregnant or breast-feeding, ask a health professional before use.

Keep out of reach of children. In case of accidental overdose, contact a doctor or Poison Control Center immediately. Prompt
medical attention is critical for adults as well as for children even if
you do not notice any signs or symptoms. Do not exceed recommended dosage

Inactive Ingredients

Cornstarch, polyethylene glycol, stearic acid, povidone

Directions

Adults and Children Take 2 tablets every 4 to 6 hours as

12 years of age needed. Do not take more than 12 tablets

or older in 24 hours.

Children 6-11 years Take 1 tablet every 4 to 6 hours as

of age needed. Do not take more than 5

tablets in 24 hours.

Children under 6 Do not use this regular strength product.

years of age This will provide more than the

recommended dose (overdose) and could

cause serious health problems.

STORAGE AND HANDLING

Store at 59-86 degree F (15-30 degree C)

GENERAL PRECAUTIONS

tamper evident sealed packets; do not use any open or torn packets

DESCRIPTION

Distributed by GENUINE FIRST AID
600 Cleveland Str Suite 400, Clearwater, FL 33755